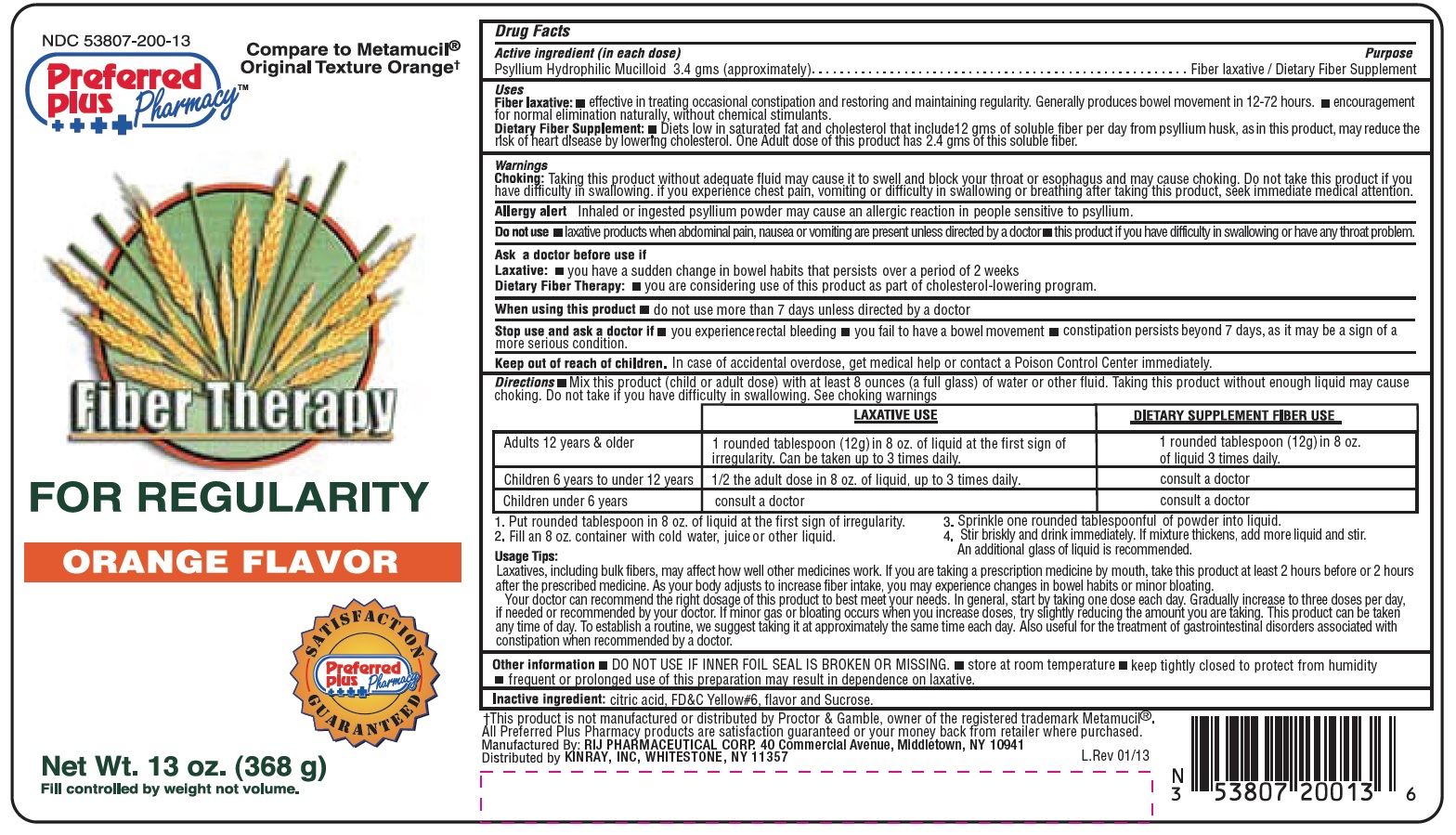 DRUG LABEL: Fiber Therapy Orange Flavor
                
NDC: 53807-200 | Form: GRANULE, FOR SOLUTION
Manufacturer: Rij Pharmaceutical Corporation
Category: otc | Type: HUMAN OTC DRUG LABEL
Date: 20180430

ACTIVE INGREDIENTS: PSYLLIUM HUSK 3.4 g/100 g
INACTIVE INGREDIENTS: SUCROSE; CITRIC ACID MONOHYDRATE; FD&C YELLOW NO. 6

Drug Facts

Active Ingredients (in each dose)

Psyllium Hydrophilic Mucilloid 3.4 gms (approximately)

Purpose

Fiber laxative / Dietary Fiber Supplement

Uses

Fiber laxative

- effective in treating occasional constipation and restoring and maintaining regularity. Generally produces bowel movement in 12-72 hours
- encouragement for normal elimination naturally, without chemical stimulants

Dietary FIber Supplement

- Diets low in saturated fat and cholesterol that includes 12 gms of soluble fiber per day from psyllium husk, as in this product, may reduce the risk of heart disease by lowering cholesterol. One Adult dose of this product has 2.4 gms of this soluble fiber.

Warnings

Choking

- Taking this product without adequate fluid may cause it to swell and block your throat or esophagus and may cause choking. Do not take this product if you have difficulty in swallowing. If you experience chest pain, vomiting or difficulty in swallowing or breathing after taking this product, seek immediate medical attention

Allergy alert

- Inhaled or ingested psyllium powder may cause allergic reaction in people sensitive to psyllium

Do not use

- laxative products when abdominal pain, nausea or vomitting are present unless directed by a doctor
- this product if you have difficulty in swallowing or have any throat problem.

Ask a doctor before use if

Laxative

- you have a sudden change in bowel habits that persists over a period of 2 weeks

Dietary Fiber Therapy

- you are considering use of this product as part of cholesterol-lowering program.

When using this product

- do not use more than 7 days unless directed by a doctor

Stop use and ask a doctor if

- you experince rectal bleeding
- you faile to have bowel movement
- constipation persists beyond 7 days, as it may be a sign of a more serious condition.

Keep out of reach of children

In case of accidental overdose, get medical help or contact a Poison Control Center immediately.

Directions

Mix this product (child or adult dose) with at least 8 ounces (a full glass) of water or other fluid. Taking this product with enough liquid may cause choking. Do not take if you have difficulty in swallowing. See choking warnings

 | LAXATIVE USE | DIETARY SUPPLEMENT FIBER USE
Adults 12 years & older | 1 rounded teaspoon (7gms) in 8 oz. of liquid at the first sign of irregularity. Can be taken up to 3 times daily | 1 rounded teaspoon (12 gms) in 8 oz. of liquid 3 times daily.
Children 6 years to under 12 years | 1/2 the adult dose in 8 oz. of liquid, up to 3 times daily | consult a doctor
Children under 6 years | consult a doctor | consult a doctor

1. Put rounded teaspoon in 8 oz. of liquid at the first sign of irregularity.
2. Fill an 8 oz. container with cold water, juice or other liquid.
3. Sprinkle one rounded teaspoondul of powder into liquid.
4. Stir briskly and drink immediately. If mixture thickens, add more liquid and stir. An additional glass of liquid is recommended.

Usage Tips:

Laxatives, including bulk fibers, may affect how well other medicines work. If you are taking a prescription medicine by mouth, take this product at least 2 hours before or 2 hours after the prescribed medicine. As your boday adjusts to increase fiber intake, you may experience changes in bowel habits or minor bloating.

Your doctor can recommend the right dosage of this product to best meet your needs. In general, start by taking one dose a day. Gradually increase to three doses per day, if needed or recommeded by your doctor. If minor gas or bloating occurs when you increrase doses, try slightly reducing the amount your are taking. This product can be taken any time of day. To establish a routine, we suggest taking it at approximately the same time each day. Also useful for the treatment of gastrointestinal disorders associated with consitipation when recommended by a doctor.

Other information

- DO NOT USE IF INNER FOIL SEAL IS BROKEN OR MISSING.
- store at room temperature
- keep tightly closed to protect from humidity
- frequent or prolonged use of this prepartion may result in dependence on laxative.

Inactive Ingredients

citric acid, FD&C Yellow#6, flavor and Sucrose